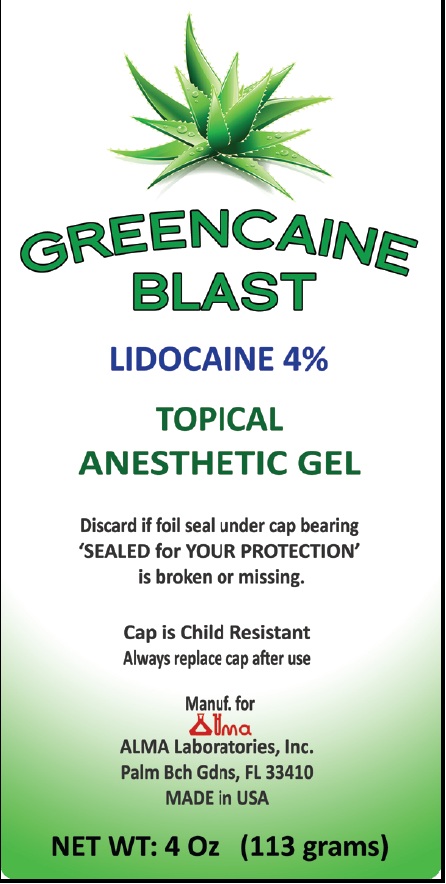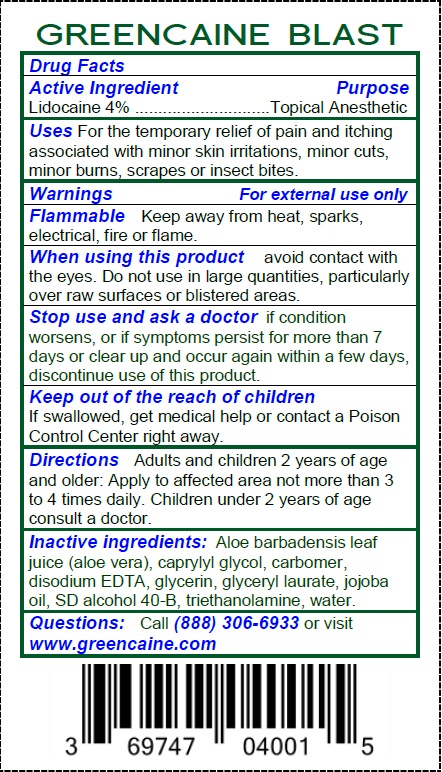 DRUG LABEL: Greencaine Blast
NDC: 69747-040 | Form: GEL
Manufacturer: ALMA Laboratories, Inc.
Category: otc | Type: HUMAN OTC DRUG LABEL
Date: 20231212

ACTIVE INGREDIENTS: LIDOCAINE 40 mg/1 g
INACTIVE INGREDIENTS: CAPRYLYL GLYCOL; CARBOXYPOLYMETHYLENE; EDETATE DISODIUM ANHYDROUS; GLYCERIN; GLYCERYL LAURATE; JOJOBA OIL; TROLAMINE; WATER

Greencaine Blast

Drug Facts

Lidocaine 4%

Active Ingredient

Lidocaine 4%

Purpose

Topical Anesthetic

Uses

For the temporary relief of pain and itching associated with minor skin irritations, minor cuts, minor burns, scrapes or insect bites.

Warnings

For external use only

Flammable

Keep away from heat, sparks, electrical, fire or flame.

When using this product

avoid contact with the eyes. Do not use in large quantities, particularly over raw surfaces or blistered areas.

Stop use and ask a doctor

if condition worsens, or if symptoms persist for more than 7 days or clear up and occur again within a few days, discontinue use of this product.

Keep out of the reach of children

If swallowed, get medical helo or contact a Poison Control Center right away.

Directions

Adults and children 2 years of age and older: Apply to affected area not more than 3 to times daily. Children under 2 years of age consult a doctor.

Inactive ingredients:

Aloe barbadensis leaf juice (aloe vera), caprylyl glycol, carbomer, disodium EDTA, glycerin, glyceryl laurate, jojoba oil, SD alcohol 40-B, trithanolamine, water.

Questions:

Call or visit (888) 306-6933 www.greencaine.com